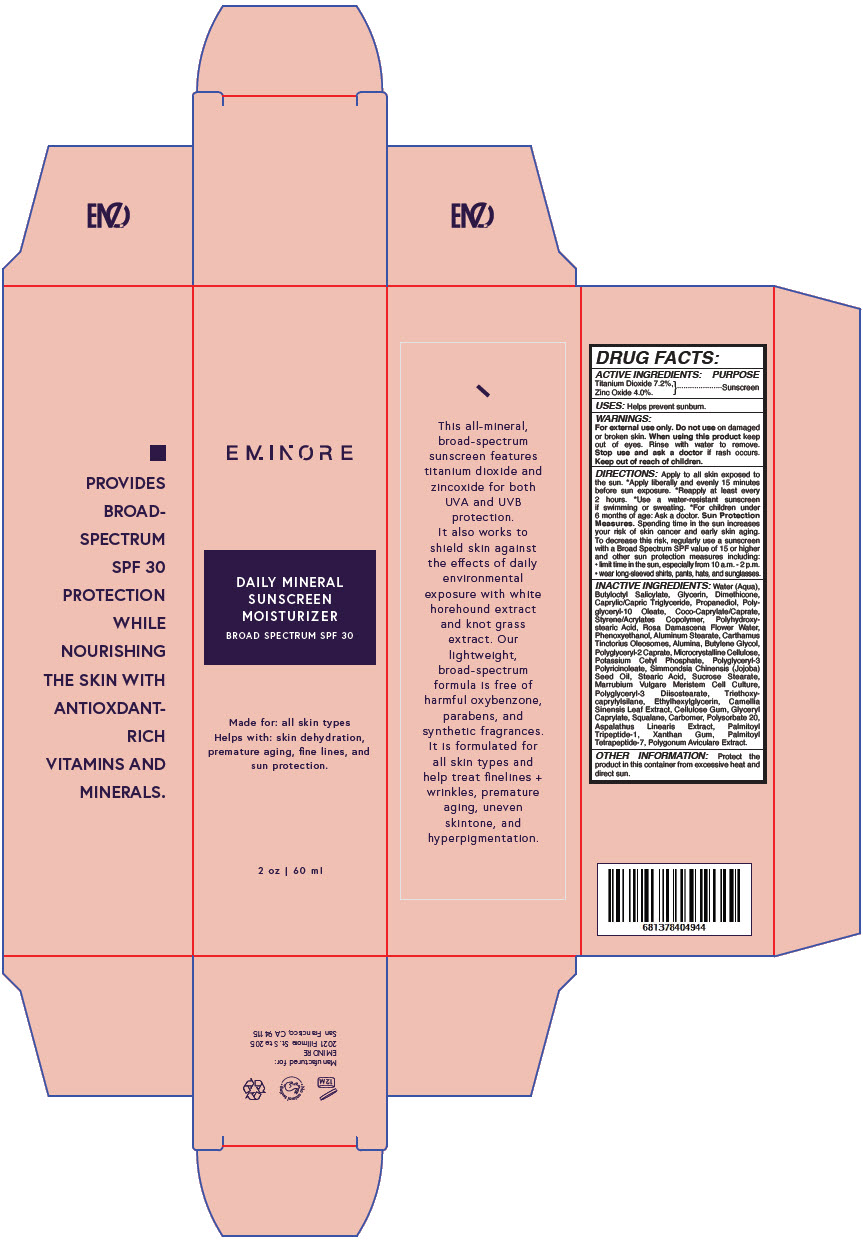 DRUG LABEL: EMINORE -  Daily Mineral Sunscreen Moisturizer Broad Spectrum SPF 30
NDC: 66163-2703 | Form: LIQUID
Manufacturer: Cosmetic Solutions LLC
Category: otc | Type: HUMAN OTC DRUG LABEL
Date: 20220218

ACTIVE INGREDIENTS: Titanium Dioxide 7.2 g/100 mL; Zinc Oxide 4 g/100 mL
INACTIVE INGREDIENTS: Water; Butyloctyl Salicylate; Glycerin; Dimethicone; Medium-Chain Triglycerides; Propanediol; Polyglyceryl-10 Oleate; Cocoyl Caprylocaprate; Rosa X Damascena Flower Oil; Phenoxyethanol; Aluminum Stearate; Carthamus Tinctorius Seed Oleosomes; Aluminum Oxide; Butylene Glycol; Polyglyceryl-2 Caprate; Microcrystalline Cellulose; Potassium Cetyl Phosphate; Polyglyceryl-3 Pentaricinoleate; Jojoba Oil; Stearic Acid; Sucrose Stearate; Polyglyceryl-3 Diisostearate; Triethoxycaprylylsilane; Ethylhexylglycerin; Green Tea Leaf; Carboxymethylcellulose Sodium, Unspecified; Glyceryl Monocaprylate; Squalane; Carbomer Homopolymer, Unspecified Type; Polysorbate 20; Palmitoyl Tripeptide-1; Xanthan Gum; Palmitoyl Tetrapeptide-7; Polygonum Aviculare Top

EMINORE - Daily Mineral Sunscreen Moisturizer Broad Spectrum SPF 30

DRUG FACTS

ACTIVE INGREDIENTS

Titanium Dioxide 7.2%, Zinc Oxide 4.0%.

PURPOSE

Sunscreen

USES

Helps prevent sunburn.

WARNINGS

For external use only. Do not use on damaged or broken skin. When using this product keep out of eyes. Rinse with water to remove. Stop use and ask a doctor if rash occurs.

Keep out of reach of children.

DIRECTIONS

Apply to all skin exposed to the sun. *Apply liberally and evenly 15 minutes before sun exposure. *Reapply at least every 2 hours. *Use a water-resistant sunscreen if swimming or sweating. *For children under 6 months of age: Ask a doctor. Sun Protection Measures. Spending time in the sun increases your risk of skin cancer and early skin aging. To decrease this risk, regularly use a sunscreen with a Broad Spectrum SPF value of 15 or higher and other sun protection measures including:

- limit time in the sun, especially from 10 a.m. - 2 p.m.
- wear long-sleeved shirts, pants, hats, and sunglasses.

INACTIVE INGREDIENTS

Water (Aqua), Butyloctyl Salicylate, Glycerin, Dimethicone, Caprylic/Capric Triglyceride, Propanediol, Polyglyceryl-10 Oleate, Coco-Caprylate/Caprate, Styrene/Acrylates Copolymer, Polyhydroxystearic Acid, Rosa Damascena Flower Water, Phenoxyethanol, Aluminum Stearate, Carthamus Tinctorius Oleosomes, Alumina, Butylene Glycol, Polyglyceryl-2 Caprate, Microcrystalline Cellulose, Potassium Cetyl Phosphate, Polyglyceryl-3 Polyricinoleate, Simmondsia Chinensis (Jojoba) Seed Oil, Stearic Acid, Sucrose Stearate, Marrubium Vulgare Meristem Cell Culture, Polyglyceryl-3 Diisostearate, Triethoxycaprylylsilane, Ethylhexylglycerin, Camellia Sinensis Leaf Extract, Cellulose Gum, Glyceryl Caprylate, Squalane, Carbomer, Polysorbate 20, Aspalathus Linearis Extract, Palmitoyl Tripeptide-1, Xanthan Gum, Palmitoyl Tetrapeptide-7, Polygonum Aviculare Extract.

OTHER INFORMATION

Protect the product in this container from excessive heat and direct sun.

PRINCIPAL DISPLAY PANEL - 60 ml Bottle Carton

EMINORE

DAILY MINERAL
SUNSCREEN
MOISTURIZER
BROAD SPECTRUM SPF 30

Made for: all skin types
Helps with: skin dehydration,
premature aging, fine lines, and
sun protection.

2 oz | 60 ml